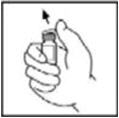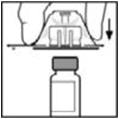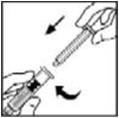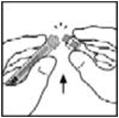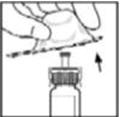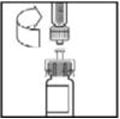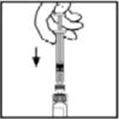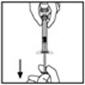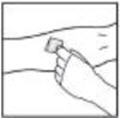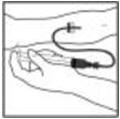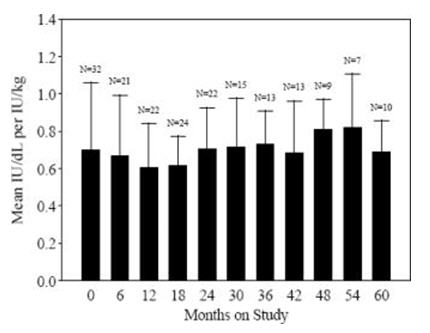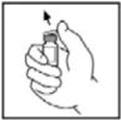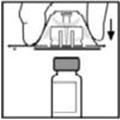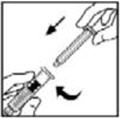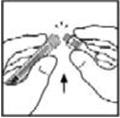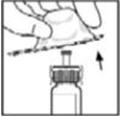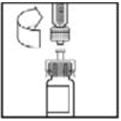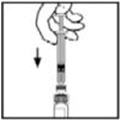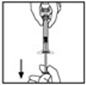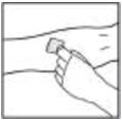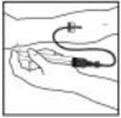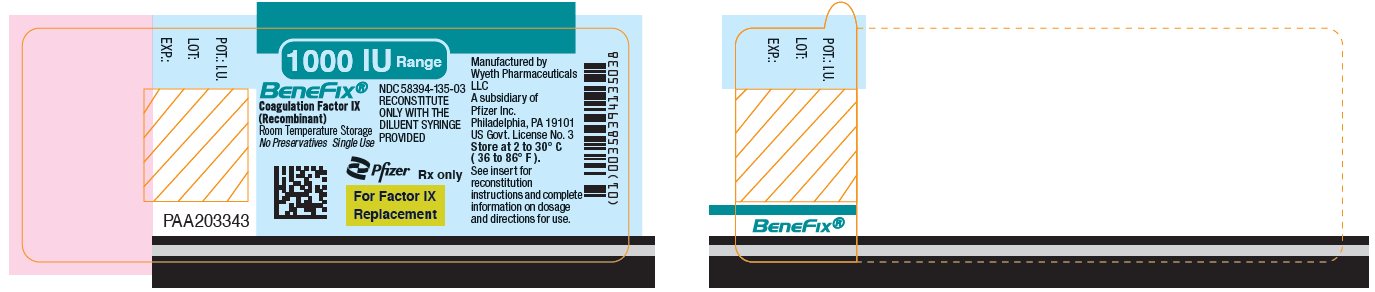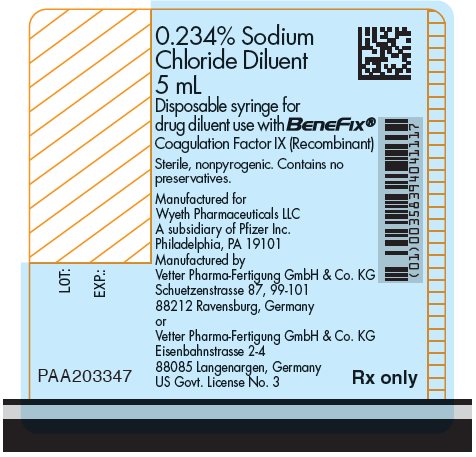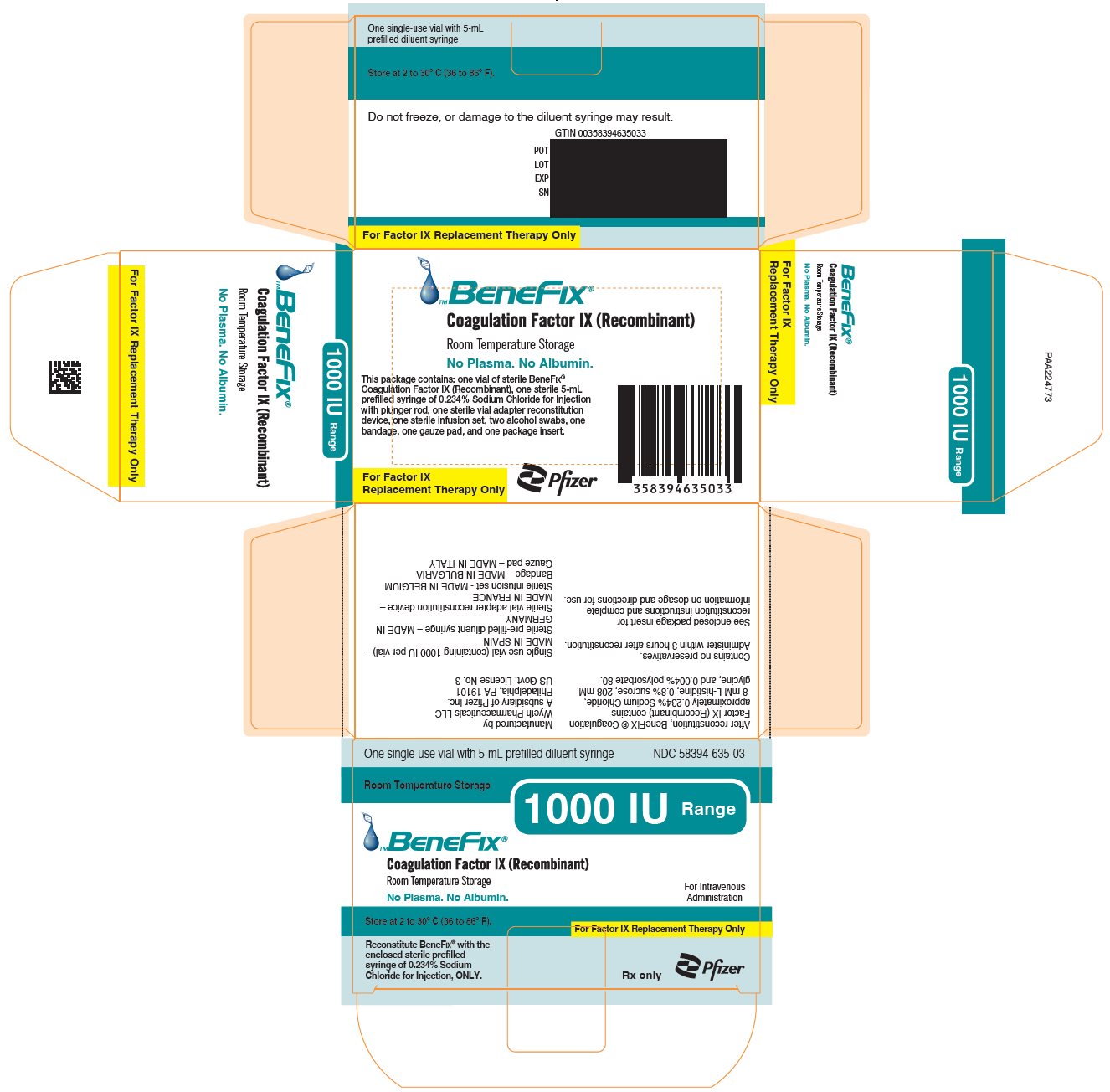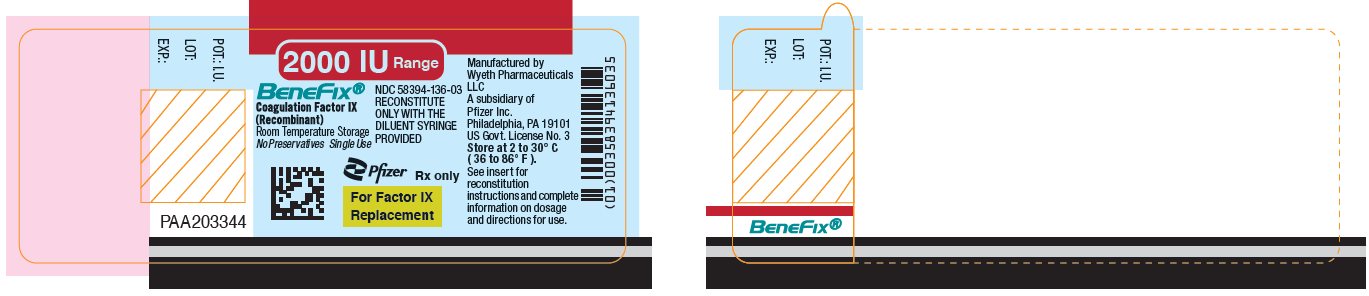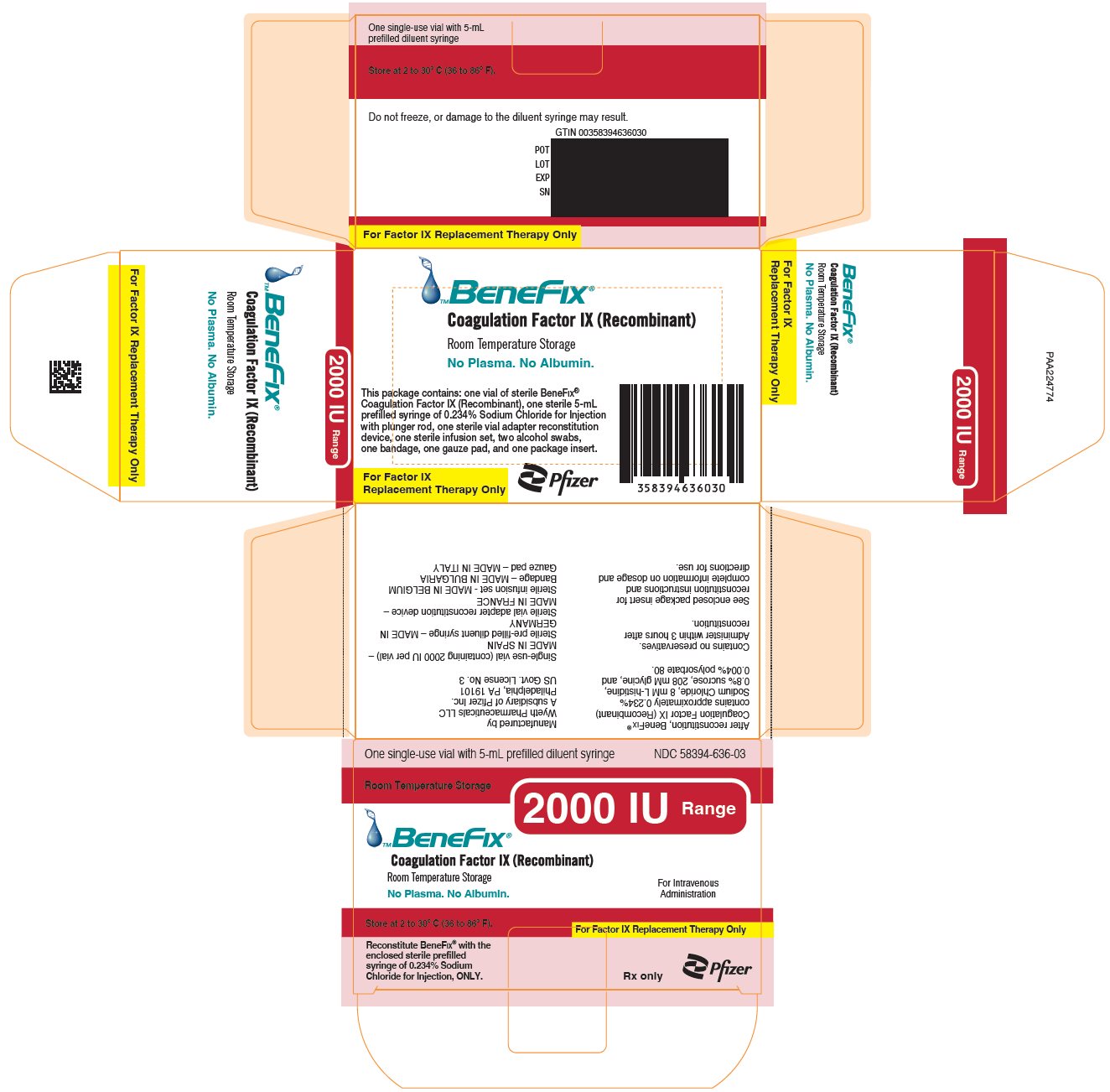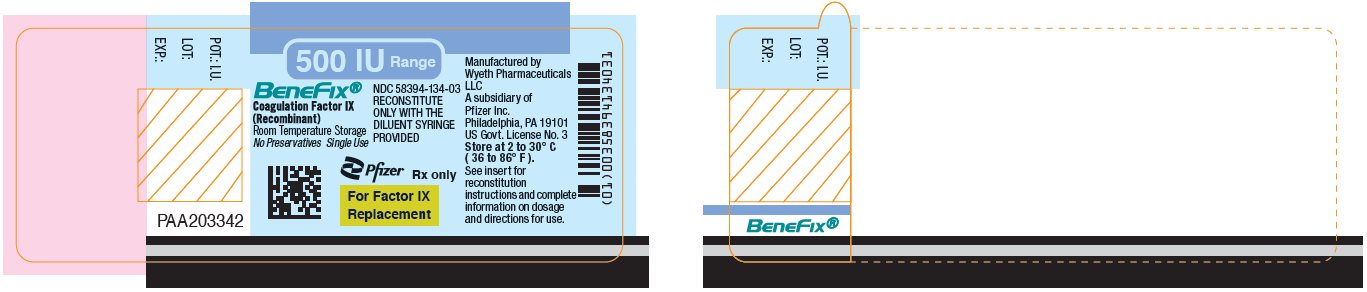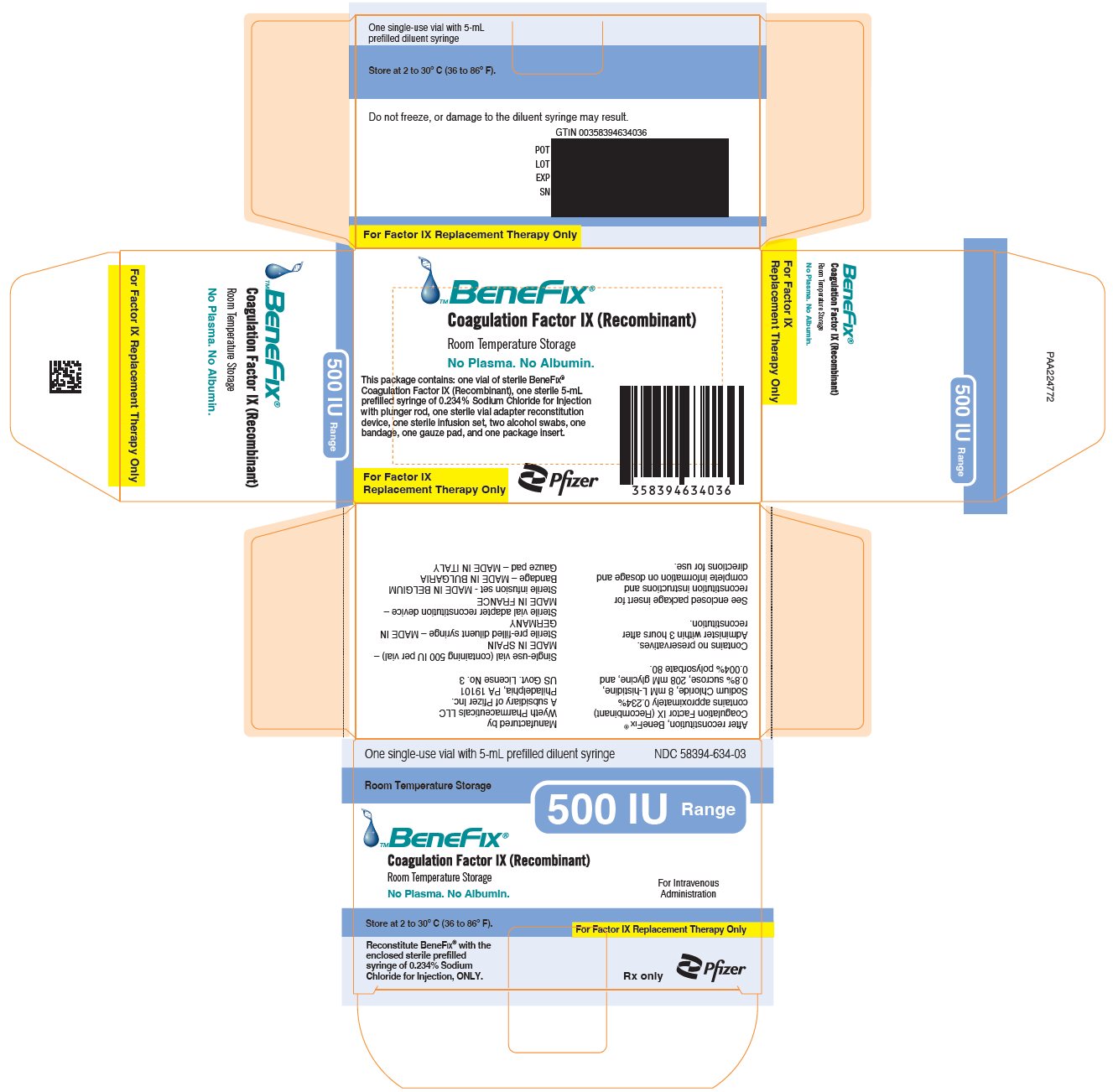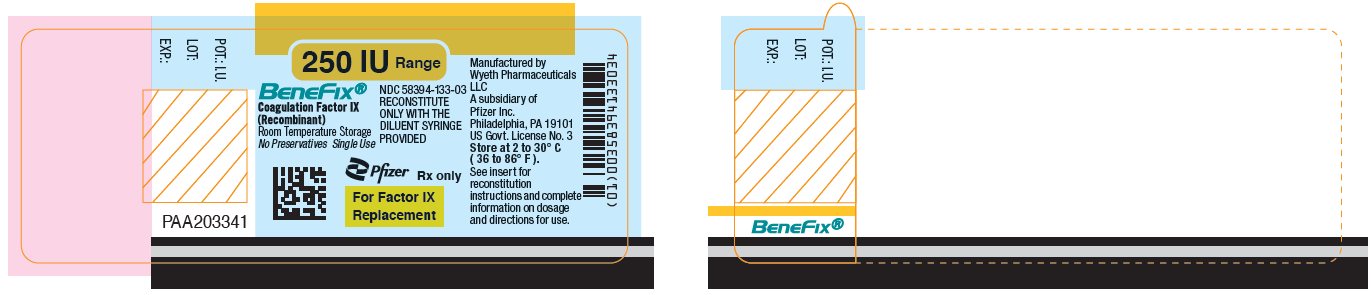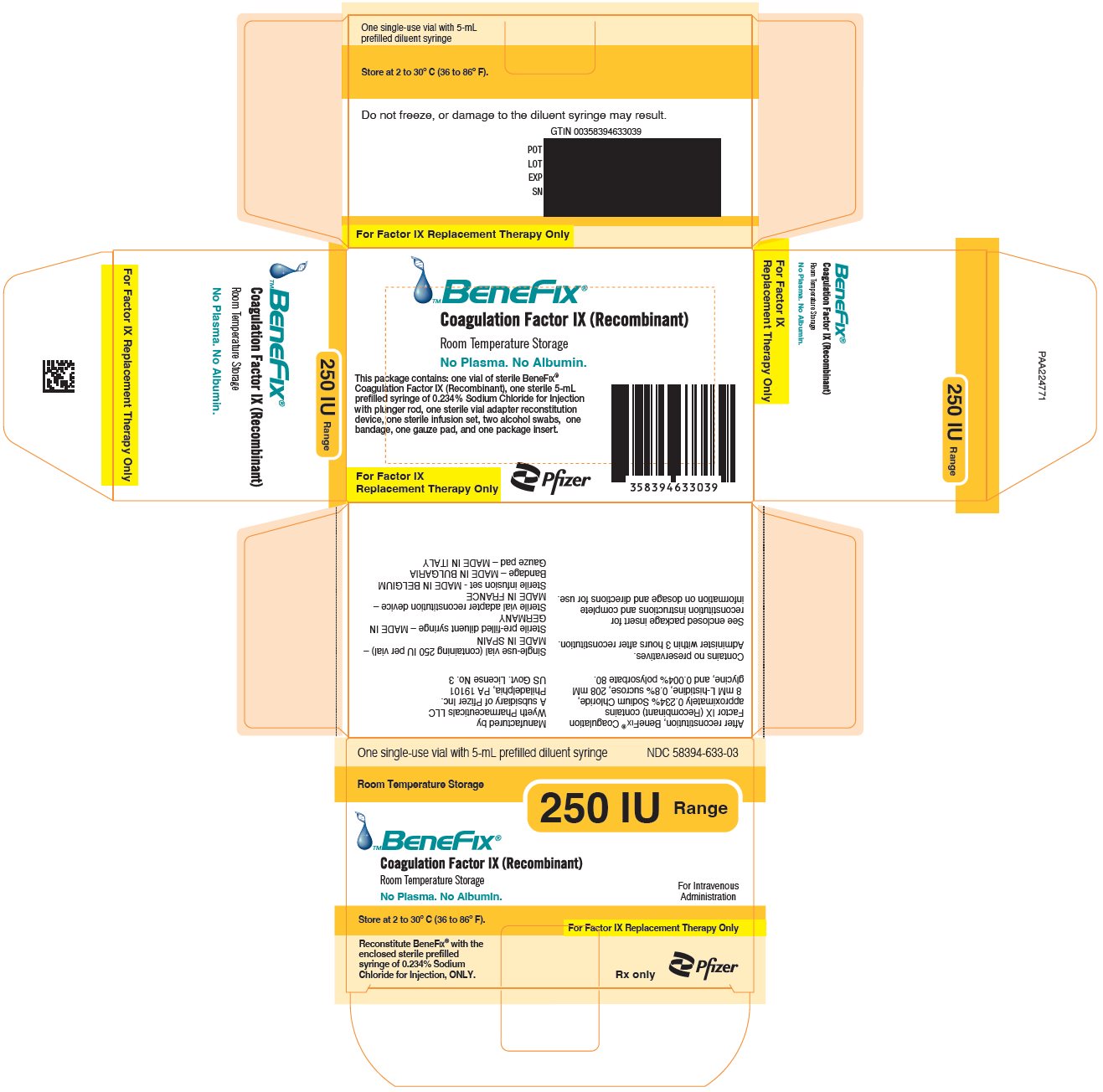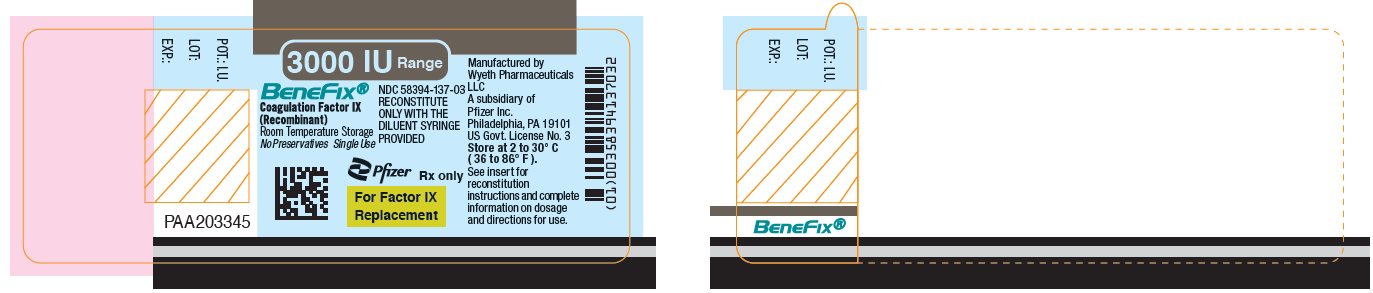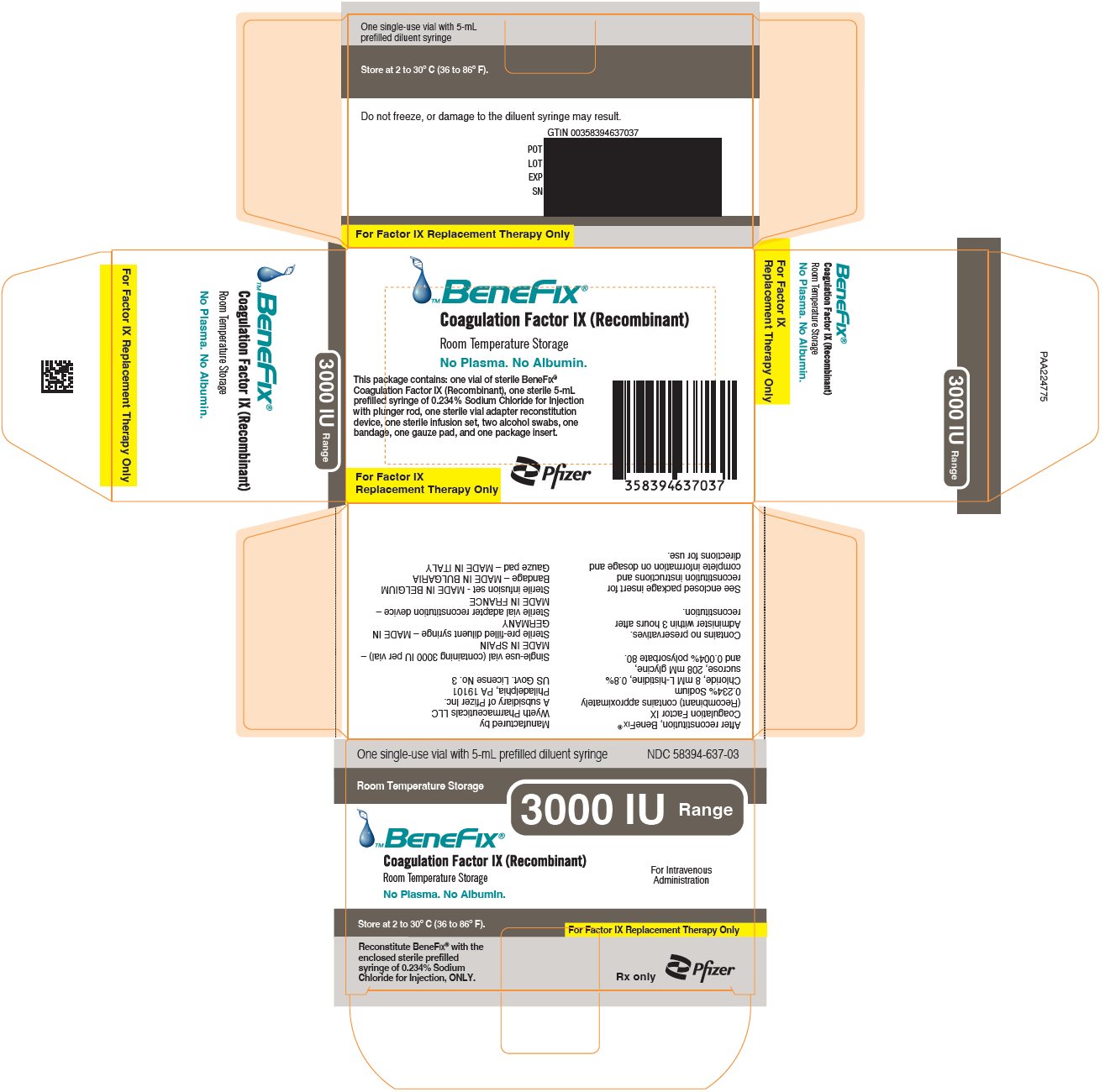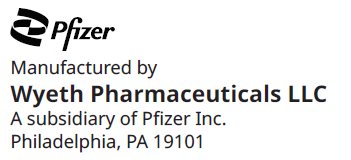 DRUG LABEL: BeneFIX
NDC: 58394-635 | Form: KIT | Route: INTRAVENOUS
Manufacturer: Wyeth BioPharma Division of Wyeth Pharmaceuticals LLC
Category: other | Type: PLASMA DERIVATIVE
Date: 20250224

ACTIVE INGREDIENTS: COAGULATION FACTOR IX RECOMBINANT HUMAN 1000 [iU]/5 mL; ISOPROPYL ALCOHOL 70 mL/100 mL
INACTIVE INGREDIENTS: HISTIDINE 6.2 mg/5 mL; GLYCINE 78.1 mg/5 mL; SUCROSE 40 mg/5 mL; POLYSORBATE 80 0.22 mg/5 mL; SODIUM CHLORIDE 11.93 mg/5 mL; WATER 5 mL/5 mL; WATER

HIGHLIGHTS OF PRESCRIBING INFORMATION

These highlights do not include all the information needed to use BeneFIX safely and effectively. See full prescribing information for BeneFIX.
BeneFIX® [coagulation factor IX (recombinant)]
lyophilized powder for solution, for intravenous use
Initial U.S. Approval: 1997

1 INDICATIONS AND USAGE

BeneFIX is a recombinant human blood coagulation factor IX indicated for adults and children with hemophilia B (congenital factor IX deficiency or Christmas disease) for:

- On-demand treatment and control of bleeding episodes. (1)
- Perioperative management of bleeding. (1)
- Routine prophylaxis to reduce the frequency of bleeding episodes. (1)

Limitations of Use

BeneFIX is not indicated for induction of immune tolerance in patients with hemophilia B. (1)

2 DOSAGE AND ADMINISTRATION

For intravenous use after reconstitution only.

- One international unit (IU) of BeneFIX per kilogram of body weight increased the circulating activity of factor IX as follows:
  - Adolescents/Adults (≥12 years): 0.8 ± 0.2 IU/dL (range 0.4 to 1.2 IU/dL). (2.1)
  - Children (<12 years): 0.7 ± 0.3 IU/dL (range 0.2 to 2.1 IU/dL). (2.1)
- Determine the initial estimated dose using the following formula:

Required units = | body weight (kg) × desired factor IX increase (IU/dL or % of normal) × reciprocal of observed recovery (IU/kg per IU/dL). (2.1)

- Dosage and duration of treatment with BeneFIX depend on the severity of the factor IX deficiency, the location and extent of bleeding, and the patient's clinical condition, age and recovery of factor IX. (2)
- Routine Prophylaxis:
  For long-term prophylaxis against bleeding, the recommended regimen is 100 IU/kg once weekly. Adjust the dosing regimen (dose or frequency) based on the patient's clinical response. (2.1)

3 DOSAGE FORMS AND STRENGTHS

BeneFIX is available as lyophilized powder in single-use vials containing nominally 250, 500, 1000, 2000, or 3000 IU. (3)

4 CONTRAINDICATIONS

Do not use in patients who have manifested life-threatening, immediate hypersensitivity reactions, including anaphylaxis, to the product or its components, including hamster protein. (4)

5 WARNINGS AND PRECAUTIONS

- Hypersensitivity reactions, including anaphylaxis, are possible. Should symptoms occur, discontinue treatment with the product and seek emergency treatment. Patients may develop hypersensitivity to hamster (CHO) protein as BeneFIX contains trace amounts. (5.1)
- BeneFIX has been associated with the development of thromboembolic complications, including in patients receiving continuous infusion through a central venous catheter. (5.2)
- Nephrotic syndrome has been reported following immune tolerance induction with factor IX products in hemophilia B patients with factor IX inhibitors and a history of allergic reactions to factor IX. (5.3)
- Development of neutralizing antibodies (inhibitors) to BeneFIX may occur. If expected plasma factor IX activity levels are not attained, or if patient presents with allergic reaction, or if bleeding is not controlled with an expected dose, perform an assay that measures factor IX inhibitor concentration. (5.4)

6 ADVERSE REACTIONS

The most common adverse reactions (incidence >5%) from clinical trials were fever, cough, nausea, injection site reaction, injection site pain, headache, dizziness and rash. (6)

To report SUSPECTED ADVERSE REACTIONS, contact Wyeth Pharmaceuticals LLC at 1-800-934-5556 or FDA at 1-800-FDA-1088 or www.fda.gov/medwatch.

8 USE IN SPECIFIC POPULATIONS

Pediatric Use: Lower recovery, shorter half-life and higher clearance (based on kg body weight) have been observed in children (<12 years). Dose adjustment may be needed. (8.4, 12.3)

FULL PRESCRIBING INFORMATION

1 INDICATIONS AND USAGE

BeneFIX®, Coagulation Factor IX (Recombinant), is a human blood coagulation factor indicated in adults and children with hemophilia B (congenital factor IX deficiency or Christmas disease) for:

- On-demand treatment and control of bleeding episodes
- Perioperative management of bleeding
- Routine prophylaxis to reduce the frequency of bleeding episodes

Limitation of Use

BeneFIX is not indicated for induction of immune tolerance in patients with hemophilia B [see Warnings and Precautions (5.3)].

2 DOSAGE AND ADMINISTRATION

For intravenous use after reconstitution only.

- Each vial of BeneFIX has the recombinant Factor IX (rFIX) potency in the International Units (IU) stated on the vial.
- Initiate treatment under the supervision of a physician experienced in the treatment of hemophilia B.
- Dosage and duration of treatment with BeneFIX depend on the severity of the factor IX deficiency, the location and extent of bleeding, and the patient's clinical condition, age and recovery of factor IX.
- Dosing of BeneFIX may differ from that of plasma-derived factor IX products [see Clinical Pharmacology (12)]. Subjects at the low end of the observed factor IX recovery may require upward dosage adjustment of BeneFIX to as much as two times (2X) the initial empirically calculated dose in order to achieve the intended rise in circulating factor IX activity.
- Monitor patients using a factor IX activity assay to ensure that the desired factor IX activity level has been achieved. Titrate the dose using the factor IX activity, pharmacokinetic parameters, such as half-life and recovery, as well as taking the clinical situation into consideration in order to adjust the dose as appropriate.

2.1 Dose

Calculating Initial Dose

Use the following formula to calculate the initial dose of BeneFIX:

number of factor IX IU required (IU) | = | body weight (kg) | × | desired factor IX increase (% of normal or IU/dL) | × | reciprocal of observed recovery (IU/kg per IU/dL)

Average Recovery

Adolescents/Adults (≥12 years)

In adults, on average, one International Unit (IU) of BeneFIX per kilogram of body weight increased the circulating activity of factor IX by 0.8 ± 0.2 IU/dL (range 0.4 to 1.2 IU/dL). Use the following formula to estimate the dose with 0.8 IU/dL average increase of factor IX per IU/kg body weight administered:

number of factor IX IU required (IU) | = | body weight (kg) | × | desired factor IX increase (% of normal or IU/dL) | × | 1.3 (IU/kg per IU/dL)

Children (<12 years)

In children, on average, one international unit of BeneFIX per kilogram of body weight increased the circulating activity of factor IX by 0.7 ± 0.3 IU/dL (range 0.2 to 2.1 IU/dL; median of 0.6 IU/dL per IU/kg). Use the following formula to estimate the dose with 0.7 IU/dL average increase of factor IX per IU/kg body weight administered:

number of factor IX IU required (IU) | = | body weight (kg) | × | desired factor IX increase (% of normal or IU/dL) | × | 1.4 (IU/kg per IU/dL)

Doses administered should be titrated to the patient's clinical response. Patients may vary in their pharmacokinetic (e.g., half-life, recovery) and clinical responses to BeneFIX. Although the dose can be estimated by the calculations above, it is highly recommended that, whenever possible, appropriate laboratory tests, including serial factor IX activity assays, be performed.

Dosing for On-demand Treatment and Control of Bleeding Episodes and Perioperative Management

Table: 1
Type of Hemorrhage | Circulating Factor IX Activity Required [% of normal or (IU/dL)] | Dosing Interval [hours] | Duration of Therapy [days]
Minor; Uncomplicated hemarthroses, superficial muscle, or soft tissue | 20-30 | 12-24 | 1-2
Moderate; Intramuscle or soft tissue with dissection, mucous membranes, dental extractions, or hematuria | 25-50 | 12-24 | Treat until bleeding stops and healing begins, about 2 to 7 days
Major; Pharynx, retropharynx, retroperitoneum, CNS, surgery | 50-100 | 12-24 | 7-10

Adapted from: Roberts and Eberst^1.

Routine Prophylaxis

For long-term prophylaxis against bleeding, the recommended regimen is 100 IU/kg once weekly. Children (<12 years) have lower recovery, shorter half-life and higher clearance (based on per kg body weight) as compared to adolescents and adults. Adjust the dosing regimen (dose or frequency) based on the patient's clinical response.

2.2 Preparation and Reconstitution

The procedures below are provided as general guidelines for the preparation and reconstitution of BeneFIX.

Preparation

1. Always wash hands before performing the following procedures.
2. Use aseptic technique (meaning clean and germ-free) during the reconstitution procedure.
3. Use all components in the reconstitution and administration of this product as soon as possible after opening their sterile containers to minimize unnecessary exposure to the atmosphere.
4. Pooling: If needing more than one vial of BeneFIX per infusion, reconstitute each vial according to the following instructions. Remove the diluent syringe leaving the vial adapter in place, and use a separate large luer lock syringe to draw back the reconstituted contents of each vial. Do not detach the diluent syringes or the large luer lock syringe until you are ready to attach the large luer lock syringe to the next vial adapter.

Reconstitution

1. If refrigerated, allow the vial of lyophilized BeneFIX and the pre-filled diluent syringe to reach room temperature.
2. Remove the plastic flip-top cap from the BeneFIX vial to expose the central portions of the rubber stopper.
3. Wipe the top of the vial with the alcohol swab provided, or use another antiseptic solution, and allow to dry. After cleaning, do not touch the rubber stopper with your hand or allow it to touch any surface.
4. Peel back the cover from the clear plastic vial adapter package. Do not remove the adapter from the package.
5. Place the vial on a flat surface. While holding the adapter in the package, place the vial adapter over the vial and press down firmly on the package until the adapter spike penetrates the vial stopper.
6. Grasp the plunger rod as shown in the diagram. Avoid contact with the shaft of the plunger rod. Attach the threaded end of the plunger rod to the diluent syringe plunger by pushing and turning firmly.
7. Break off the tamper-resistant plastic-tip cap from the diluent syringe by snapping the perforation of the cap. Do not touch the inside of the cap or the syringe tip. The diluent syringe may need to be recapped (if not administering reconstituted BeneFIX immediately), so place the cap on its top on a clean surface in a spot where it would be least likely to become environmentally contaminated.
8. Lift the package away from the adapter and discard the package.
9. Place the vial on a flat surface. Connect the diluent syringe to the vial adapter by inserting the tip into the adapter opening while firmly pushing and turning the syringe clockwise until secured.
10. Slowly depress the plunger rod to inject all the diluent into the BeneFIX vial.
11. Without removing the syringe, gently swirl the contents of the vial until the powder is dissolved.
12. Invert the vial and slowly draw the solution into the syringe.
13. Detach the syringe from the vial adapter by gently pulling and turning the syringe counter-clockwise. Discard the vial with the adapter attached.
14. The reconstituted solution should be clear and colorless. If it is not, discard and use a new kit. If the solution is not to be used immediately, recap the syringe. Do not touch the syringe tip or the inside of the cap.
15. Store the reconstituted solution at room temperature and use it within 3 hours.

Note: BeneFIX, when reconstituted, contains polysorbate-80, which is known to increase the rate of di-(2-ethylhexyl) phthalate (DEHP) extraction from polyvinyl chloride (PVC). This should be considered during the preparation and administration of BeneFIX, including storage time elapsed in a PVC container following reconstitution. It is important that the recommendations for dosage and administration be followed closely [see Dosage and Administration (2.1, 2.3)].

Note: The tubing of the infusion set included with this kit does not contain DEHP.

2.3 Administration

For intravenous use after reconstitution only.

The safety and efficacy of administration by continuous infusion have not been established [see Warnings and Precautions (5.2)].

- Inspect BeneFIX solution for particulate matter and discoloration prior to administration, whenever solution and container permit.
- Administer BeneFIX using the tubing provided in this kit, and the pre-filled diluent syringe provided, or a single sterile disposable plastic syringe.
- Do not mix or administer BeneFIX in the same tubing or container with other medicinal products.

Administration

1. Attach the syringe to the luer end of the infusion set tubing provided.
2. Apply a tourniquet and prepare the injections site by wiping the skin well with an alcohol swab provided in the kit.
3. Perform venipuncture. Insert the needle on the infusion set tubing into the vein, and remove the tourniquet. Inject the reconstituted BeneFIX intravenously over several minutes. Adjust the rate of administration based on the patient's comfort level.
  Note: Agglutination of red blood cells in the tubing/syringe has been reported with the administration of BeneFIX. No adverse events have been reported in association with this observation. To minimize the possibility of agglutination, it is important to limit the amount of blood entering the tubing. Blood should not enter the syringe. If red blood cell agglutination is observed in the tubing or syringe, discard all material (tubing, syringe and BeneFIX solution) and resume administration with a new package.
4. Following completion of BeneFIX treatment, remove and discard the infusion set. Dispose of all unused solution, empty vial(s), and used needles and syringes in an appropriate container.

3 DOSAGE FORMS AND STRENGTHS

BeneFIX is supplied as a white lyophilized powder in the following nominal dosages:

- 250 IU
- 500 IU
- 1000 IU
- 2000 IU
- 3000 IU

Each BeneFIX single-use vial has the actual recombinant factor IX (rFIX) potency in the IU stated on the vial.

4 CONTRAINDICATIONS

BeneFIX is contraindicated in patients who have manifested life-threatening, immediate hypersensitivity reactions, including anaphylaxis, to the product or its components, including hamster protein.

5 WARNINGS AND PRECAUTIONS

5.1 Hypersensitivity Reactions

Hypersensitivity reactions, including anaphylaxis, have been reported with BeneFIX and have manifested as pruritus, rash, urticaria, hives, facial swelling, dizziness, hypotension, nausea, chest discomfort, cough, dyspnea, wheezing, flushing, discomfort (generalized) and fatigue. Frequently, these events have occurred in close temporal association with the development of factor IX inhibitors.

Closely monitor patients for signs and symptoms of acute hypersensitivity reactions, particularly during the early phases of initial exposure to product. Because of the potential for allergic reactions with factor IX concentrates, perform the initial (approximately 10 – 20) administrations of factor IX under medical supervision where proper medical care for allergic reactions could be provided. Advise patients to discontinue use of the product and contact their physician and/or seek immediate emergency care. Immediately discontinue the administration and initiate appropriate treatment if symptoms occur.

BeneFIX contains trace amounts of hamster (CHO) proteins. Patients treated with this product may develop hypersensitivity to these non-human mammalian proteins.

5.2 Thromboembolic Complications

There have been post-marketing reports of thrombotic events in patients receiving continuous-infusion BeneFIX through a central venous catheter, including life-threatening superior vena cava (SVC) syndrome in critically ill neonates [see Adverse Reactions (6.2)]. The safety and efficacy of BeneFIX administration by continuous infusion have not been established [see Dosage and Administration (2.1, 2.3)].

5.3 Nephrotic Syndrome

Nephrotic syndrome has been reported following immune tolerance induction with factor IX products in hemophilia B patients with factor IX inhibitors and a history of allergic reactions to factor IX. The safety and efficacy of using BeneFIX for immune tolerance induction have not been established.

5.4 Neutralizing Antibodies (Inhibitors)

Neutralizing antibodies (inhibitors) have been reported following administration of BeneFIX [see Adverse Reactions (6.1)]. Evaluate patients using BeneFIX for the development of factor IX inhibitors by appropriate clinical observations and laboratory tests. If expected plasma factor IX activity levels are not attained, or if bleeding is not controlled with an expected dose, perform an assay that measures factor IX inhibitor concentration.

Patients with factor IX inhibitors are at an increased risk of severe hypersensitivity reactions or anaphylaxis upon subsequent challenge with factor IX.^2 Evaluate patients experiencing allergic reactions for the presence of an inhibitor and closely monitor patients with inhibitors for signs and symptoms of acute hypersensitivity reactions, particularly during the early phases of initial exposure to product [see Warnings and Precautions (5.1)].

5.5 Monitoring Laboratory Tests

- Monitor patients for factor IX activity levels by the one-stage clotting assay to confirm that adequate factor IX levels have been achieved and maintained, when clinically indicated [see Dosage and Administration (2.1)].
- Monitor patients for the development of inhibitors if expected plasma factor IX activity levels are not attained, or if bleeding is not controlled with the recommended dose of BeneFIX. Determine plasma factor IX inhibitor levels in Bethesda Units (BUs).

6 ADVERSE REACTIONS

The most serious adverse reactions are systemic hypersensitivity reactions, including bronchospastic reactions and/or hypotension and anaphylaxis and the development of high-titer inhibitors necessitating alternative treatments to factor IX replacement therapy.

The most common adverse reactions observed in clinical trials [frequency >5% of previously treated patients (PTPs) or previously untreated patients (PUPs)] were fever, cough, headaches, dizziness, nausea, injections site reaction, injection site pain and skin-related hypersensitivity reactions (e.g., rash, hives).

6.1 Clinical Trials Experience

Because clinical trials are conducted under widely varying conditions, adverse reaction rates observed in the clinical trials of a drug cannot be directly compared to rates in the clinical trials of another drug and may not reflect the rates observed in clinical practice.

During uncontrolled, open-label clinical trials with BeneFIX conducted in PTPs, 113 adverse reactions with known or unknown relation to BeneFIX therapy were reported among 38.5% (25 of 65) of subjects (with some subjects reporting more than one event) who received a total of 7,573 infusions. These adverse reactions are summarized in Table 2.

Table 2: Adverse Reactions Reported for PTPs [Adverse reactions reported within 72 hours of an infusion of BeneFIX.]
Body System | Adverse Reaction | Number of Patients (%)
Blood and lymphatic system disorders | Factor IX inhibition [Low-titer transient inhibitor formation.] | 1 (1.5%)
Eye disorders | Blurred vision | 1 (1.5%)
Gastrointestinal disorders | Nausea | 4 (6.2%)
 | Vomiting | 1 (1.5%)
General disorders and administration site conditions | Injection site reaction | 5 (7.7%)
 | Injection site pain | 4 (6.2%)
 | Fever | 2 (3.1%)
Infections and infestations | Cellulitis at IV site | 1 (1.5%)
 | Phlebitis at IV site | 1 (1.5%)
Nervous system disorders | Headache | 7 (10.8%)
 | Dizziness | 5 (7.7%)
 | Taste perversion (altered taste) | 3 (4.6%)
 | Shaking | 1 (1.5%)
 | Drowsiness | 1 (1.5%)
Renal and urinary disorders | Renal infarct [The renal infarct developed in a hepatitis C antibody-positive patient 12 days after a dose of BeneFIX for a bleeding episode. The relationship of the infarct to the prior administration of BeneFIX is uncertain.] | 1 (1.5%)
Respiratory, thoracic and mediastinal disorders | Dry cough | 1 (1.5%)
 | Hypoxia | 1 (1.5%)
 | Chest tightness | 1 (1.5%)
Skin and subcutaneous disorders | Rash | 4 (6.2%)
 | Hives | 2 (3.1%)
Vascular disorders | Flushing | 2 (3.1%)

In the 63 PUPs, who received a total of 5,538 infusions, 10 adverse reactions were reported among 9.5% of the patients (6 out of 63) having known or unknown relationship to BeneFIX. These events are summarized in Table 3.

Table 3: Adverse Reactions Reported for PUPs [Adverse reactions reported within 72 hours of an infusion of BeneFIX.]
Body System | Adverse Reaction | Number of Patients (%)
Blood and lymphatic system disorders | Factor IX inhibition [Two subjects developed high-titer inhibitor formation during treatment with BeneFIX.] | 2 (3.2%)
General disorders and administration site conditions | Injection site reaction | 1 (1.6%)
 | Chills | 1 (1.6%)
Respiratory, thoracic and mediastinal disorders | Dyspnea (respiratory distress) | 2 (3.2%)
Skin and subcutaneous disorders | Hives | 3 (4.8%)
 | Rash | 1 (1.6%)

In a multi-center, prospective, open-label clinical trial with BeneFIX administered at 100 IU/kg once weekly, 25 PTPs (exposed to a factor IX containing product for ≥100 exposure days) were evaluated, with 25 subjects treated for approximately 52 weeks. Common (≥5%) adverse reactions were headache (36%), fever (20%), and cough (8%). No subject was withdrawn from the trial due to an adverse reaction. In the trial, no inhibitors were detected and no thrombotic events or anaphylactic reactions were reported.

Immunogenicity

In clinical trials with 65 PTPs (defined as having more than 50 exposure days), a low-titer inhibitor was observed in one patient. The inhibitor was transient, the patient continued on the trial and had normal factor IX recovery at the trial completion (approximately 15 months after inhibitor detection).

In clinical trials with pediatric PUPs, inhibitor development was observed in 2 out of 63 patients (3.2%), both were high-titer (>5 BU) inhibitors detected after 7 and 15 exposure days, respectively. Both patients were withdrawn from the trial.

In a clinical trial of 25 PTPs, with BeneFIX administered at 100 IU/kg once weekly, no inhibitors were detected.

The detection of antibody formation is highly dependent on the sensitivity and specificity of the assay. Additionally, the observed incidence of antibody (including neutralizing antibody) positivity in an assay may be influenced by several factors, including assay methodology, sample handling, timing of sample collection, concomitant medications, and underlying disease. For these reasons, comparison of the incidence of antibodies to BeneFIX with the incidence of antibodies to other products may be misleading.

Thromboembolic complications

All subjects participating in the PTP, PUP and surgery trials were monitored for clinical evidence of thrombosis. No thrombotic complications were reported in PUPs or surgery subjects. One PTP subject experienced a renal infarct (see Table 2). Laboratory studies of thrombogenicity (fibrinopeptide A and prothrombin fragment 1 + 2) were obtained in 41 PTPs and 7 surgery subjects prior to infusion and up to 24 hours following infusion. The results of these studies were inconclusive. Out of 29 PTP subjects noted to have elevated fibrinopeptide A levels post-infusion of BeneFIX, 22 also had elevated levels at baseline. Surgery subjects showed no evidence of significant increase in coagulation activation.

6.2 Postmarketing Experience

The following post-marketing adverse reactions have been reported for BeneFIX: inadequate factor IX recovery, inadequate therapeutic response, inhibitor development [see Clinical Pharmacology (12)], anaphylaxis [see Warnings and Precautions (5.1)], angioedema, dyspnea, hypotension, and thrombosis.

Because these reactions are reported voluntarily from a population of uncertain size, it is not always possible to reliably estimate their frequency or establish a causal relationship to drug exposure.

There have been post-marketing reports of thrombotic events, including life-threatening SVC syndrome in critically ill neonates, while receiving continuous-infusion BeneFIX through a central venous catheter. Cases of peripheral thrombophlebitis and DVT have also been reported. In some, BeneFIX was administered via continuous infusion, which is not an approved method of administration [see Dosage and Administration (2)]. The safety and efficacy of BeneFIX administration by continuous infusion have not been established [see Warnings and Precautions (5.2)].

8 USE IN SPECIFIC POPULATIONS

8.1 Pregnancy

Risk Summary

There are no data with BeneFIX use in pregnant women to inform a drug-associated risk. Animal reproduction studies have not been conducted with BeneFIX. It is not known whether BeneFIX can affect reproductive capacity or cause fetal harm when given to pregnant women.

In the U.S. general population, the estimated background risk of major birth defect and miscarriage in clinically recognized pregnancies is 2–4% and 15–20%, respectively.

8.2 Lactation

Risk Summary

There is no information regarding the presence of BeneFIX in human milk, the effect on the breastfed infant, and the effects on milk production. The developmental and health benefits of breastfeeding should be considered along with the mother's clinical need for BeneFIX and any potential adverse effects on the breastfed child from BeneFIX or from the underlying maternal condition.

8.4 Pediatric Use

Safety, efficacy, and pharmacokinetics of BeneFIX have been evaluated in previously treated (PTP) and previously untreated pediatric patients (PUP) [see Clinical Studies (14) and Adverse Reactions (6)]. On average, lower recovery, shorter half-life and higher clearance (based on kg body weight) have been observed in children younger than 12 years old [see Clinical Pharmacology (12.3)]. Dose adjustment may be needed [see Dosage and Administration (2.1)].

8.5 Geriatric Use

Clinical trials of BeneFIX did not include sufficient numbers of subjects aged 65 and over to determine whether they respond differently from younger subjects. Dose selection for an elderly patient should be individualized [see Dosage and Administration (2.1)].

11 DESCRIPTION

BeneFIX, Coagulation Factor IX (Recombinant), is a purified protein produced by recombinant DNA technology. The product is formulated as a sterile, non-pyrogenic, lyophilized powder preparation intended to be reconstituted for intravenous injection. It is available in single-use vials containing the labeled amount of factor IX activity, expressed in International Units (IU). Each vial contains nominally 250, 500, 1000, 2000, or 3000 IU of recombinant coagulation factor IX. The potency (in IU) is determined using an in vitro one-stage clotting assay against the World Health Organization (WHO) International Standard for Factor IX concentrate. One IU is the amount of factor IX activity present in 1 mL of pooled, normal human plasma. After reconstitution of the lyophilized drug product, the concentrations of excipients are 0.234% sodium chloride, 8 mM L-histidine, 0.8% sucrose, 208 mM glycine, 0.004% polysorbate 80. The specific activity of BeneFIX is greater than or equal to 200 IU per milligram of protein. BeneFIX contains no preservatives and all dosage strengths yield a clear, colorless solution upon reconstitution.

Coagulation factor IX is the active ingredient in BeneFIX. It has a primary amino acid sequence that is identical to the Ala^148 allelic form of human factor IX, and has structural and functional characteristics similar to those of endogenous factor IX.

BeneFIX is not derived from human blood. It is produced by a genetically engineered Chinese hamster ovary (CHO) cell line that is extensively characterized. No additives of animal or human origin are used during the cell culture, purification, and formulation processes of BeneFIX. The stored cell banks are free of human blood or plasma products. The CHO cell line secretes recombinant factor IX into a defined cell culture medium, and the recombinant factor IX is purified by a four-step chromatography purification process that does not require a monoclonal antibody step. The process also includes a membrane nanofiltration step that has the ability to retain molecules with apparent molecular weights >70,000 Da (such as large proteins and viral particles). BeneFIX is a single component by SDS-polyacrylamide gel electrophoresis evaluation.

12 CLINICAL PHARMACOLOGY

12.1 Mechanism of Action

BeneFIX temporarily replaces the missing clotting factor IX that is needed for effective hemostasis.

12.2 Pharmacodynamics

The activated partial thromboplastin time (aPTT) is prolonged in people with hemophilia B. Treatment with factor IX concentrate may normalize the aPTT by temporarily replacing the factor IX. The administration of BeneFIX increases plasma levels of factor IX, and can temporarily correct the coagulation defect in these patients.

12.3 Pharmacokinetics

In a randomized, cross-over pharmacokinetic study, BeneFIX reconstituted in 0.234% sodium chloride diluent was shown to be pharmacokinetically equivalent to the previously marketed BeneFIX (reconstituted with Sterile Water for Injection) in 24 previously treated patients (≥12 years) at a dose of 75 IU/kg. In addition, pharmacokinetic parameters were followed up in 23 previously treated patients after repeated administration of BeneFIX for six months and found to be unchanged compared with those obtained at the initial evaluation. A summary of pharmacokinetic data are presented in Table 4:

Table 4: Pharmacokinetic Parameter Estimates for BeneFIX (75 IU/kg) at Baseline and Month 6 in Previously Treated Patients with Hemophilia B
Parameter | Baseline N = 24 Mean ± SD | Month 6 N = 23 Mean ± SD
Cmax (IU/dL) | 54.5 ± 15.0 | 57.3 ± 13.2
AUC∞ (IU∙hr/dL) | 940 ± 237 | 923 ± 205
t1/2 (hr) | 22.4 ± 5.3 | 23.8 ± 6.5
CL (mL/hr/kg) | 8.47 ± 2.12 | 8.54 ± 2.04
Recovery (IU/dL per IU/kg) | 0.73 ± 0.20 | 0.76 ± 0.18
Abbreviations: AUC∞ = area under the plasma concentration-time curve from time zero to infinity; Cmax = peak concentration; t1/2 = plasma elimination half-life; CL = clearance; SD = standard deviation.

Pediatric Patients (<12 years)

A population pharmacokinetic model was developed using data collected in patients aged 7 months to 60 years who received single doses of BeneFIX ranging from 50 to 75 IU/kg. The parameters estimated using the final 2-compartment model are shown in Table 5. Infants and children had higher clearance, larger volume of distribution, shorter half-life and lower recovery than adolescents and adults.

Table 5: Mean ± SD Pharmacokinetic Parameters Derived from Population Pharmacokinetic Analysis
Age Group | Infants (<2 years) | Children 2 to <6 yr | Children 6 to <12 yr | Adolescents and Adults (≥12 years)
Number of subjects | 7 | 16 | 1 | 43
Clearance (mL/h/kg) | 13.1 ± 2.1 | 13.1 ± 2.8 | 15.5 | 8.4 ± 2.4
Vss (mL/kg) | 252 ± 35 | 257 ± 25 | 303 | 229 ± 57
Half-life (h) | 15.6 ± 1.2 | 16.7 ± 1.9 | 16.3 | 23.1 ± 4.4
Recovery (IU/dL per IU/kg) | 0.61 ± 0.10 | 0.60 ± 0.08 | 0.47 | 0.72 ± 0.19
Abbreviations: SD = standard deviation; Vss = volume of distribution at steady-state.

Data from 57 PUP subjects who underwent repeat recovery testing for up to 60 months demonstrated that the average recovery was consistent over time, as shown in Figure 1.

Figure 1. Average Recovery over Time

13 NONCLINICAL TOXICOLOGY

13.1 Carcinogenesis, Mutagenesis, Impairment of Fertility

BeneFIX has been shown to be nonmutagenic in the Ames assay and non-clastogenic in a chromosomal aberrations assay. No investigations on carcinogenesis or impairment of fertility have been conducted.

14 CLINICAL STUDIES

Efficacy of BeneFIX has been evaluated in clinical trials in which a total of 153 subjects received BeneFIX either for the on-demand treatment and control of bleeding episodes, perioperative management, and routine prophylaxis in patients with hemophilia B.

On-demand Treatment and Control of Bleeding Episodes

Fifty-six PTPs and sixty-three PUPs were treated for bleeding episodes on an on-demand treatment and control of bleeds (see Tables 6 and 7). The PTPs were followed over a median interval of 24 months (mean 23.4 ± 5.3 months) and for a median of 83.5. The PUPs were followed over a median interval of 37 months (mean 38.1 ± 16.4 months) and for a median of 89 exposure days.

Fifty-five PTPs and fifty-four PUPs received BeneFIX for the treatment of bleeding episodes (see Table 6). Bleeding episodes that were managed successfully included hemarthrosis and bleeding in soft tissue and muscle. Data concerning the severity of bleeding episodes were not reported. In the PTPs, 88% of total infusions administrated for on-demand treatment were rated as an "excellent" or "good" response.

Table 6: Efficacy of BeneFIX for On-Demand Treatment in PTPs and PUPs
 | Median Dose: IU/kg (range) | Rate of Bleeds Resolved with 1 Infusion | Response to 1st Infusion Rating [Response ratings not provided for 1.3% and 2% of 1st infusions for PTPs and PUPs, respectively.]; Excellent/Good | Response to 1st Infusion Rating; Moderate | Response to 1st Infusion Rating; No Response
PTPs; N = 55 [One subject discontinued the trial after one month of treatment due to bleeding episodes that were difficult to control; he did not have a detectable inhibitor.] | 42.8 (6.5–224.6) | 81% | 90.9% | 7.1% | 0.7%
PUPs; N = 54 [Three subjects were not successfully treated including one episode in a subject due to delayed time to infusion and insufficient dosing and in 2 subjects due to inhibitor formation.] | 62.7 (8.2–292) | 75% | 94.1% | 2.9% | 1.0%

A total of 20 PTPs were treated with BeneFIX for secondary prophylaxis (the regular administration of FIX replacement therapy to prevent bleeding in patients who may have already demonstrated clinical evidence of hemophilic arthropathy or joint disease) at some regular interval during the trial with a mean of 2 infusions per week (see Table 7). Thirty-two PUPs were administered BeneFIX for routine (primary and secondary) prophylaxis (see Table 7). Twenty-four PUPs were administered BeneFIX at least twice weekly, and eight PUPs were administered BeneFIX once weekly. Seven PTPs experienced a total of 26 spontaneous bleeding episodes within 48 hours after an infusion. Six spontaneous bleeds within 48 hours after an infusion were reported in 5 PUPs. Prophylaxis therapy was rated as "excellent" or "effective" in 93% of PTPs receiving prophylaxis one to two times per week.

Table 7: Efficacy of Prophylaxis of BeneFIX in PTPs and PUPs
Total Exposure (infusions) | Duration of Prophylaxis (months) (mean ± SD) | Dose IU/kg (mean ± SD) | Spontaneous Bleeds Within 48 hrs of Infusion | Response Rating [Response ratings provided at approximately 3-month intervals. In total, 116 and 172 assessments reported for PTPs and PUPs, respectively. Response ratings not provided for 2.6% and 0.6% of intervals for PTPs and PUPs, respectively.] Excellent | Response Rating Effective | Response Rating Inadequate
20 PTPs
2985 | 18.2 ± 8.4 [N = 19.] | 40.3 ± 15.2 | 28 | 56.0% | 37.1% | 4.3%
32 PUPs
3158 | 14.4 ± 8.1 | 73.3 ± 33.1 | 6 | 91.3% | 6.4% | 1.7%
Abbreviation: SD = standard deviation.

Perioperative Management

Management of hemostasis was evaluated in the surgical setting in both PTPs and PUPs (see Table 8 and Table 9). Thirty-six surgical procedures have been performed in 28 PTPs with 23 major surgical procedures performed (including 6 complicated dental extractions). Thirty surgical procedures have been performed in 23 PUPs. Twenty-eight of these procedures were considered minor. Hemostasis was maintained throughout the surgical period; however, one PTP subject required evacuation of a surgical wound-site hematoma, and another PTP subject who received BeneFIX after a tooth extraction required further surgical intervention due to oozing at the extraction site. There was no clinical evidence of thrombotic complications in any of the subjects.

Among the PTP surgery subjects, the median increase in circulating factor IX activity was 0.7 IU/dL per IU/kg infused (range 0.3–1.2 IU/dL; mean 0.8 ± 0.2 IU/dL per IU/kg). The median elimination half-life for the PTP surgery subjects was 19.4 hours (range 10–37 hours; mean 21.3 ± 8.1 hours).

Table 8: Efficacy of BeneFIX for Surgical Procedures in Previously Treated Patients
Surgery Type [Some surgery types were done as a part of a single procedure.] | Number of Procedures (Number of Subjects) | Response; Excellent/Good | Response; Moderate | Response; No Response
Ankle surgery | 2 (2) | 2 (100%) | - | -
Hip prosthesis implant (right) | 1 (1) | 1 (100%) | - | -
Knee arthroplasty (2 bilateral, 1 right) | 3 (3) | 3 (100%) | - | -
Knee arthroscopic synovectomy | 2 (2) [Response assessment not provided for 1 procedure.] | 1 (50%) | - | -
Liver transplantation (orthotopic) | 1 (1) | 1 (100%) | - | -
Splenectomy | 1 (1) | 1 (100%) | - | -
External fixation device removal (wrist) | 1 (1) | 1 (100%) | - | -
Hernia repair | 3 (2) | 3 (100%) | - | -
Subacromial decompression (left) | 1 (1) | 1 (100%) | - | -
Calf debridement, dental extraction [Includes pulse and continuous-infusion regimens; CI counted as 1 procedure in this summary.] | 1 (1) | 1 (100%) | - | -
Lymph node removal, dental extraction | 1 (1) | 1 (100%) | - | -
Left heel cord lengthening | 1 (1) | 1 (100%) | - | -
Dental procedures [Includes complicated extractions (6), clearance, and fillings.] | 12 (11) | 11 (92%) | 1 (8%) | -
Minor procedures [E.g., punch biopsy of the skin.] | 6 (6) | 6 (100%) | - | -

Table 9: Efficacy of BeneFIX for Surgical Procedures in Previously Untreated Patients
Surgery Type [Some surgery types were done as a part of a single procedure.] | Number of Procedures (Number of Subjects) | Response; Excellent/Good | Response; Moderate | Response; No Response
Hernia repair | 2 (2) | 2 (100%) | - | -
Minor procedures [E.g., permanent venous access placement.] | 28 (21) [Response assessment not provided for 1 procedure.] | 27 (96%) | - | -

Nine of the major surgical procedures were performed in 8 PUPs using a continuous-infusion regimen. Five of the surgical procedures were performed in PUPs using a continuous-infusion regimen over 3 to 5 days. Although circulating factor IX levels targeted to restore and maintain hemostasis were achieved with both pulse replacement and continuous infusion regimens, clinical trial experience with continuous infusion of BeneFIX for perioperative management in hemophilia B has been too limited to establish the safety and clinical efficacy of administration of the product by continuous infusion.

Routine Prophylaxis

In an open-label trial of 25 patients (age range 12–54 years) comparing on-demand treatment versus prophylaxis when administered at a dose of 100 IU/kg once weekly, the annualized bleed rate (ABR) for the prophylaxis period was significantly lower (p < 0.0001) than the ABR for the on-demand period (mean ± standard deviation (SD): 3.6 ± 4.6, median: 2.0, min–max: 0–13.8 versus mean: 32.9 ± 17.4, median: 33.6, min–max: 6.1–69.0, respectively).

In an open-label crossover trial in patients aged 6–64 years, of 100 IU/kg once weekly (44 patients) and 50 IU/kg twice weekly (43 patients) with 4-month treatment periods, the ABR for the 100 IU/kg once-weekly prophylaxis period was mean 4.4 ± 10.0 episodes per year (median: 0.0, min–max: 0 – 50.5) and mean 2.8 ± 5.7 (median: 0.0, min–max: 0 – 24.1) for the 50 IU/kg twice-weekly period. Six patients aged <12 years had mean ABR of 1.6 ± 1.7 (median: 1.5, min–max: 0–3.3) in the 100 IU/kg once-weekly period, and mean ABR of 0 ± 0 (median: 0, min–max: 0–0) in the 50 IU/kg twice-weekly period.

15 REFERENCES

1. Roberts HR, Eberst ME. Current management of hemophilia B. Hematol Oncol Clin North Am. 1993;7(6):1269–1280.
2. Shapiro AD, Ragni MV, Lusher JM, et al. Safety and efficacy of monoclonal antibody purified factor IX concentrate in previously untreated patients with hemophilia B. Thromb Haemost. 1996;75(1):30–35.

16 HOW SUPPLIED/STORAGE AND HANDLING

How Supplied

BeneFIX, Coagulation Factor IX (Recombinant), is supplied in kits that include single-use vials which contain nominally 250, 500, 1000, 2000, or 3000 IU per vial with sterile pre-filled diluent syringe, vial adapter reconstitution device, sterile infusion set, and two (2) alcohol swabs, one bandage, and one gauze pad. The drug product, diluents for injection and the rest of components included within the BeneFIX 250, 500, 1000, 2000 or 3000 IU kit are not made from natural rubber and natural rubber latex. Actual factor IX activity in IU is stated on the label of each vial.

 | BeneFIX
Nominal Strengths | Color Code | Kit NDC Number
250 International Units | Yellow | 58394-633-03
500 International Units | Blue | 58394-634-03
1000 International Units | Green | 58394-635-03
2000 International Units | Red | 58394-636-03
3000 International Units | Grey | 58394-637-03

Storage and Handling

Product kit as packaged for sale

- Store BeneFIX at room temperature or under refrigeration, at a temperature of 2 to 30°C (36 to 86°F).
- Do not freeze to prevent damage to the diluent syringe.
- Do not use BeneFIX after the expiration date on the label.

Product after reconstitution

The product does not contain a preservative and should be used within 3 hours.

17 PATIENT COUNSELING INFORMATION

- Advise patients to read the FDA-approved patient labeling (Patient Information and Instructions for Use)
- Allergic-type hypersensitivity reactions are possible. Inform patients of the early signs of hypersensitivity reactions [including hives (rash with itching), generalized urticaria, tightness of the chest, wheezing, hypotension] and anaphylaxis. Advise patients to discontinue use of the product and contact their physicians if these symptoms occur.
- Advise patients to contact their physician or treatment facility for further treatment and/or assessment if they experience a lack of a clinical response to factor IX replacement therapy, as in some cases this may be a manifestation of an inhibitor.

This product's labeling may have been updated. For the most recent prescribing information, please visit www.pfizer.com.

For Medical Information about BENEFIX, please visit www.pfizermedinfo.com or call 1-800-438-1985.

FDA-Approved Patient Labeling

Patient Information

BeneFIX® / BEN-uh-fiks/

[Coagulation Factor IX (Recombinant)]

Please read this Patient Leaflet carefully before using BeneFIX and each time you get a refill. There may be new information. This Patient Leaflet does not take the place of talking with your doctor about your medical condition or your treatment.

What is BeneFIX?

BeneFIX is an injectable medicine that is used to help control and prevent bleeding in people with hemophilia B. Hemophilia B is also called congenital factor IX deficiency or Christmas disease.

BeneFIX is NOT used to treat hemophilia A.

What should I tell my doctor before using BeneFIX?

Tell your doctor and pharmacist about all of the medicines you take, including all prescription and non-prescription medicines, such as over-the-counter medicines, supplements, or herbal medicines.

Tell your doctor about all of your medical conditions, including if you:

- have any allergies, including allergies to hamsters.
- are pregnant or planning to become pregnant. It is not known if BeneFIX may harm your unborn baby.
- are breastfeeding. It is not known if BeneFIX passes into the milk and if it can harm your baby.

How should I infuse BeneFIX?

The initial administrations of BeneFIX should be administered under proper medical supervision, where proper medical care for severe allergic reactions could be provided.

See the step-by-step instructions for infusing BeneFIX at the end of this leaflet. You should always follow the specific instructions given by your doctor. The steps listed below are general guidelines for using BeneFIX. If you are unsure of the procedures, please call your doctor or pharmacist before using.

Call your doctor right away if bleeding is not controlled after using BeneFIX.

Your doctor will prescribe the dose that you should take.

Your doctor may need to test your blood from time to time.

BeneFIX should not be administered by continuous infusion.

What if I take too much BeneFIX?

Call your doctor if you take too much BeneFIX.

What are the possible side effects of BeneFIX?

Allergic reactions may occur with BeneFIX. Call your doctor or get emergency treatment right away if you have any of the following symptoms:

wheezing
difficulty breathing
chest tightness
turning blue (look at lips and gums)
fast heartbeat
swelling of the face
faintness
rash
hives

Your body can also make antibodies, called "inhibitors," against BeneFIX, which may stop BeneFIX from working properly.

Some common side effects of BeneFIX are fever, cough, nausea, injection site reaction, injection site pain, headache, dizziness and rash.

BeneFIX may increase the risk of thromboembolism (abnormal blood clots) in your body if you have risk factors for developing blood clots, including an indwelling venous catheter through which BeneFIX is given by continuous infusion. There have been reports of severe blood clotting events, including life-threatening blood clots in critically ill neonates, while receiving continuous-infusion BeneFIX through a central venous catheter. The safety and efficacy of BeneFIX administration by continuous infusion have not been established.

These are not all the possible side effects of BeneFIX.

Tell your doctor about any side effect that bothers you or that does not go away.

How should I store BeneFIX?

DO NOT FREEZE BeneFIX kit.

BeneFIX kit can be stored at room temperature (below 86°F) or under refrigeration.

Throw away any unused BeneFIX and diluent after the expiration date indicated on the label.

Freezing should be avoided to prevent damage to the pre-filled diluent syringe.

BeneFIX does not contain a preservative. After reconstituting BeneFIX, you can store it at room temperature for up to 3 hours. If you have not used it in 3 hours, throw it away.

Do not use BeneFIX if the reconstituted solution is not clear and colorless.

What else should I know about BeneFIX?

Medicines are sometimes prescribed for purposes other than those listed here. Do not use BeneFIX for a condition for which it was not prescribed. Do not share BeneFIX with other people, even if they have the same symptoms that you have.

This Patient Leaflet summarizes the most important information about BeneFIX. If you would like more information, talk with your doctor. You can ask your doctor or pharmacist for information about BeneFIX that was written for healthcare professionals.

Instructions for Use

BeneFIX® / BEN-uh-fiks/

[Coagulation Factor IX (Recombinant)]

BeneFIX is supplied as a powder. Before it can be infused in your vein (intravenous injection), you must reconstitute the powder by mixing it with the liquid diluent supplied. The liquid diluent is 0.234% sodium chloride. BeneFIX should be reconstituted and infused using the infusion set, diluent, syringe, and adapter provided in this kit, and by following the directions below.

RECONSTITUTION

Always wash your hands before performing the following steps. Try to keep everything clean and germ-free while you are reconstituting BeneFIX. Once you open the vials, you should finish reconstituting BeneFIX as soon as possible. This will help keep the infusion set materials germ-free.

Note: If you use more than one vial of BeneFIX per infusion, reconstitute each vial according to steps 1 through 13.

1. If refrigerated, let the vial of BeneFIX and the pre-filled diluent syringe reach room temperature.
2. Remove the plastic flip-top cap from the BeneFIX vial to show the center part of the rubber stopper.
3. Wipe the top of the vial with the alcohol swab provided, or use another antiseptic solution, and allow to dry. After cleaning, do not touch the rubber stopper with your hand or allow it to touch any surface.
4. Peel back the cover from the clear plastic vial adapter package. Do not remove the adapter from the package.
5. Place the vial on a flat surface. While holding the adapter in the package, place the vial adapter over the vial. Press down firmly on the package until the adapter snaps into place on top of the vial, with the adapter spike penetrating the vial stopper.
6. Grasp the plunger rod as shown in the picture below. Do not touch the shaft of the plunger rod. Attach the threaded end of the plunger rod to the diluent syringe plunger by pushing and turning firmly.
7. Break off the tamper-resistant, plastic-tip cap from the diluent syringe by snapping the perforation of the cap. Do not touch the inside of the cap or the syringe tip. The diluent syringe may need to be recapped (if reconstituted BeneFIX is not used immediately), so place the cap on its tip on a clean surface in a spot where it will stay clean.
8. Lift the package away from the adapter and discard the package.
9. Place the vial on a flat surface. Connect the diluent syringe to the vial adapter by inserting the tip of the syringe into the adapter opening while firmly pushing and turning the syringe clockwise until the connection is secured.
10. Slowly push the plunger rod to inject all the diluent into the BeneFIX vial.
11. With the syringe still connected to the adapter, gently swirl the contents of the vial until the powder is dissolved.
  Look at the final solution before infusing it. The solution should be clear to colorless. If it is not, throw away the solution and use a new kit.
12. Make sure the syringe plunger rod is still fully pressed down, then turn over the vial. Slowly pull the solution into the syringe. Turn the syringe upward again and remove any air bubbles by gently tapping the syringe with your finger and slowly pushing air out of the syringe.
  If you reconstituted more than one vial of BeneFIX, remove the diluent syringe from the vial adapter and leave the vial adapter attached to the vial. Quickly attach a separate large luer lock syringe and pull the reconstituted solution as instructed above. Repeat this procedure with each vial in turn. Do not detach the diluent syringes or the large luer lock syringe until you are ready to attach the large luer lock syringe to the next vial adapter.
13. Remove the syringe from the vial adapter by gently pulling and turning the syringe counter-clockwise. Throw away the vial with the adapter attached.
  If you are not using the solution right away, you should carefully replace the syringe cap. Do not touch the syringe tip or the inside of the cap.

BeneFIX should be infused within 3 hours after reconstitution. The reconstituted solution may be stored at room temperature prior to infusion.

INFUSION (Intravenous Injection)

Continuous infusion is not an approved way to administer BeneFIX.

Your doctor or healthcare professional should teach you how to infuse BeneFIX. Once you learn how to self-infuse, you can follow the instructions in this insert.

1. Attach the syringe to the luer end of the provided infusion set tubing.
2. Apply a tourniquet and prepare the injection site by wiping the skin well with an alcohol swab provided in the kit.
3. Insert the butterfly needle of the infusion set tubing into your vein as instructed by your doctor or healthcare provider. Remove the tourniquet. Infuse the reconstituted BeneFIX product over several minutes. Your comfort level should determine the rate of infusion.
  Clumping of red blood cells in the tubing/syringe has been reported with the administration of BeneFIX. No adverse events have been reported in association with this observation. To minimize the possibility of clumping it is important to limit the amount of blood entering the tubing. Blood should not enter the syringe.
  Note: If red blood cell clumping is observed in the tubing or syringe, discard all material (tubing, syringe and BeneFIX solution) and continue administration with a new package.
4. After infusing BeneFIX, remove the infusion set and discard. The amount of drug product left in the infusion set will not affect your treatment. Dispose of all unused solution, the empty vial(s), and the used needles and syringes in an appropriate container used for throwing away waste that might hurt others if not handled properly.

It is a good idea to record the lot number from the BeneFIX vial label every time you use BeneFIX. You can use the peel-off label found on the vial to record the lot number.

If you have any questions or concerns about BeneFIX, ask your doctor or healthcare provider.

US Govt. License No. 3

LAB-0464-15.0

PRINCIPAL DISPLAY PANEL - 5 mL Syringe Label – Used in All Kits

0.234% Sodium
Chloride Diluent
5 mL

Disposable syringe for
drug diluent use with BeneFix®
Coagulation Factor IX (Recombinant)

Sterile, nonpyrogenic. Contains no
preservatives.

Manufactured for
Wyeth Pharmaceuticals LLC
A subsidiary of Pfizer Inc.
Philadelphia, PA 19101
Manufactured by
Vetter Pharma-Fertigung GmbH & Co. KG
Schuetzenstrasse 87, 99-101
88212 Ravensburg, Germany
or
Vetter Pharma-Fertigung GmbH & Co. KG
Eisenbahnstrasse 2-4
88085 Langenargen, Germany
US Govt. License No. 3

Rx only

PRINCIPAL DISPLAY PANEL - 1000 IU Vial Label

1000 IU Range

BeneFix®
Coagulation Factor IX
(Recombinant)
NDC 58394-135-03
RECONSTITUTE
ONLY WITH THE
DILUENT SYRINGE
PROVIDED
Room Temperature Storage

No Preservatives Single Use

Pfizer
Rx only

For Factor IX
Replacement

PRINCIPAL DISPLAY PANEL - 1000 IU Kit Carton

One single-use vial with 5-mL prefilled diluent syringe
NDC 58394-635-03

Room Temperature Storage

1000 IU Range

BeneFix®
Coagulation Factor IX (Recombinant)
Room Temperature Storage
No Plasma. No Albumin.

For Intravenous
Administration

Store at 2 to 30º C (36 to 86º F).

For Factor IX Replacement Therapy Only

Reconstitute BeneFix® with the
enclosed sterile prefilled
syringe of 0.234% Sodium
Chloride for Injection, ONLY.

Rx only
Pfizer

PRINCIPAL DISPLAY PANEL - 2000 IU Vial Label

2000 IU Range

BeneFix®
Coagulation Factor IX
(Recombinant)
NDC 58394-136-03
RECONSTITUTE
ONLY WITH THE
DILUENT SYRINGE
PROVIDED
Room Temperature Storage

No Preservatives Single Use

Pfizer
Rx only

For Factor IX
Replacement

PRINCIPAL DISPLAY PANEL - 2000 IU Kit Carton

One single-use vial with 5-mL prefilled diluent syringe
NDC 58394-636-03

Room Temperature Storage

2000 IU Range

BeneFix®
Coagulation Factor IX (Recombinant)
Room Temperature Storage
No Plasma. No Albumin.

For Intravenous
Administration

Store at 2 to 30º C (36 to 86º F).

For Factor IX Replacement Therapy Only

Reconstitute BeneFix® with the
enclosed sterile prefilled
syringe of 0.234% Sodium
Chloride for Injection, ONLY.

Rx only
Pfizer

PRINCIPAL DISPLAY PANEL - 500 IU Vial Label

500 IU Range

BeneFix®
Coagulation Factor IX
(Recombinant)
NDC 58394-134-03
RECONSTITUTE
ONLY WITH THE
DILUENT SYRINGE
PROVIDED
Room Temperature Storage

No Preservatives Single Use

Pfizer
Rx only

For Factor IX
Replacement

PRINCIPAL DISPLAY PANEL - 500 IU Kit Carton

One single-use vial with 5-mL prefilled diluent syringe
NDC 58394-634-03

Room Temperature Storage

500 IU Range

BeneFix®
Coagulation Factor IX (Recombinant)
Room Temperature Storage
No Plasma. No Albumin.

For Intravenous
Administration

Store at 2 to 30º C (36 to 86º F).

For Factor IX Replacement Therapy Only

Reconstitute BeneFix® with the
enclosed sterile prefilled
syringe of 0.234% Sodium
Chloride for Injection, ONLY.

Rx only
Pfizer

PRINCIPAL DISPLAY PANEL - 250 IU Vial Label

250 IU Range

BeneFix®
Coagulation Factor IX
(Recombinant)
NDC 58394-133-03
RECONSTITUTE
ONLY WITH THE
DILUENT SYRINGE
PROVIDED
Room Temperature Storage

No Preservatives Single Use

Pfizer
Rx only

For Factor IX
Replacement

PRINCIPAL DISPLAY PANEL - 250 IU Kit Carton

One single-use vial with 5-mL prefilled diluent syringe
NDC 58394-633-03

Room Temperature Storage

250 IU Range

BeneFix®
Coagulation Factor IX (Recombinant)
Room Temperature Storage
No Plasma. No Albumin.

For Intravenous
Administration

Store at 2 to 30° C (36 to 86° F).

For Factor IX Replacement Therapy Only

Reconstitute BeneFix® with the
enclosed sterile prefilled
syringe of 0.234% Sodium
Chloride for Injection, ONLY.

Rx only
Pfizer

PRINCIPAL DISPLAY PANEL - 3000 IU Vial Label

3000 IU Range

BeneFix®
Coagulation Factor IX
(Recombinant)
NDC 58394-137-03
RECONSTITUTE
ONLY WITH THE
DILUENT SYRINGE
PROVIDED
Room Temperature Storage

No Preservatives Single Use

Pfizer
Rx only

For Factor IX
Replacement

PRINCIPAL DISPLAY PANEL - 3000 IU Kit Carton

One single-use vial with 5-mL prefilled diluent syringe
NDC 58394-637-03

Room Temperature Storage

3000 IU Range

BeneFix®
Coagulation Factor IX (Recombinant)
Room Temperature Storage
No Plasma. No Albumin.

For Intravenous
Administration

Store at 2 to 30º C (36 to 86º F).

For Factor IX Replacement Therapy Only

Reconstitute BeneFix® with the
enclosed sterile prefilled
syringe of 0.234% Sodium
Chloride for Injection, ONLY.

Rx only
Pfizer